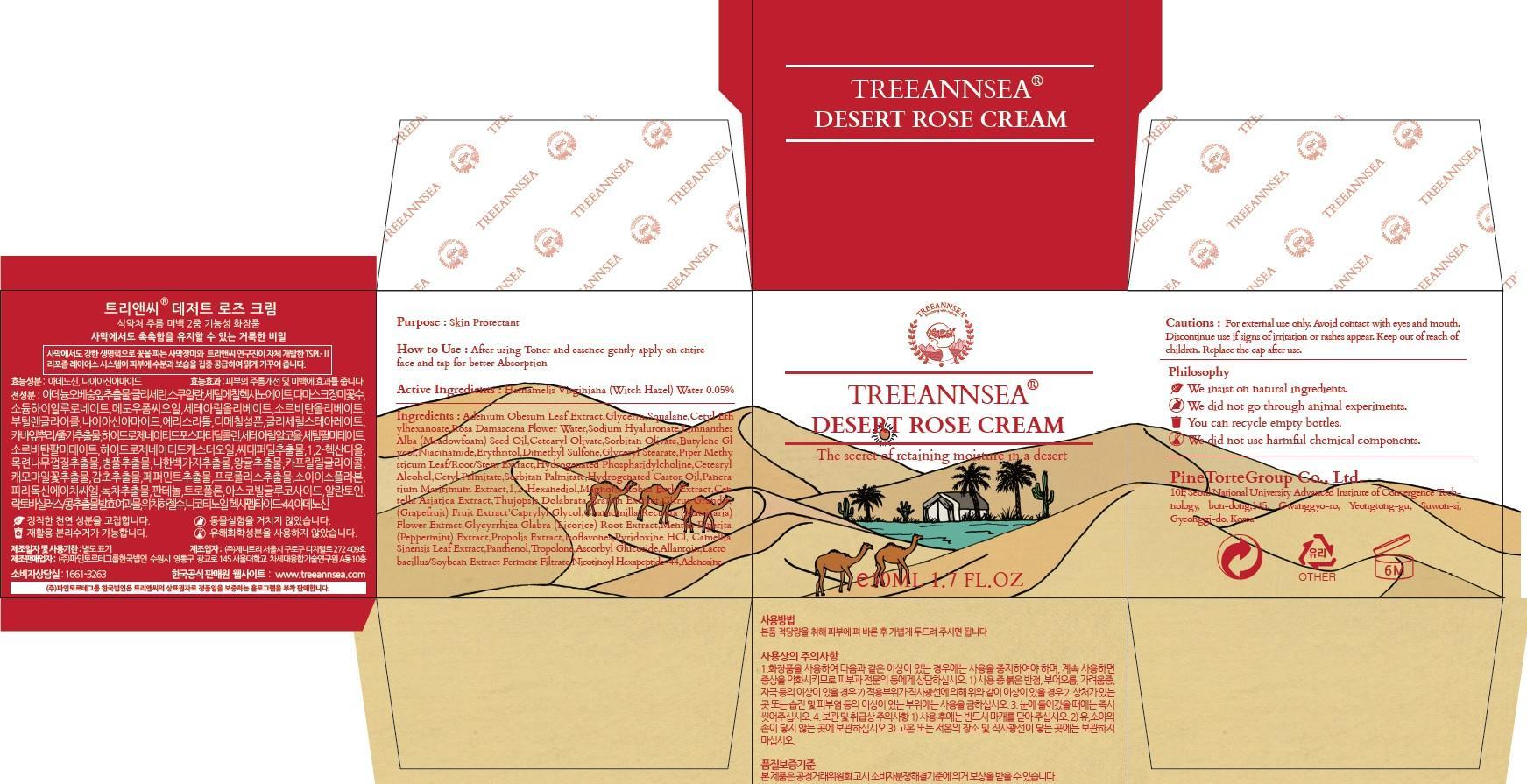 DRUG LABEL: TREEANNSEA DESERT ROSE
NDC: 69515-040 | Form: CREAM
Manufacturer: PINE TORTE GROUP CO., LTD.
Category: otc | Type: HUMAN OTC DRUG LABEL
Date: 20150319

ACTIVE INGREDIENTS: Witch Hazel 0.025 mg/50 mL
INACTIVE INGREDIENTS: Glycerin; Squalane

ACTIVE INGREDIENT

Active Ingredients: Hamamelis Virginiana (Witch Hazel) Water 0.05%

INACTIVE INGREDIENT

Inactive Ingredients: Adenium Obesum Leaf Extract, Glycerin, Squalane, Cetyl Ethylhexanoate, Rosa Damascena Flower Water, Sodium Hyaluronate, Limnanthes Alba (Meadowfoam) Seed Oil, Cetearyl Olivate, Sorbitan Olivate, Butylene Glycol, Niacinamide, Erythritol, Dimethyl Sulfone, Glyceryl Stearate, Piper Methysticum Leaf/Root/Stem Extract, Hydrogenated Phosphatidylcholine, Cetearyl Alcohol, Cetyl Palmitate, Sorbitan Palmitate, Hydrogenated Castor Oil, Pancratium Maritimum Extract, 1,2-Hexanediol, Magnolia Kobus Bark Extract, Centella Asiatica Extract, Thujopsis Dolabrata Branch Extract, Citrus Grandis (Grapefruit) Fruit Extract, Caprylyl Glycol, Chamomilla Recutita/Flower Extract, Glycyrrhiza Glabra Root Extract, Mentha Piperita (Peppermint) Extract, Propolis Extract, Isoflavones, Pyridoxine HCl, Camellia Sinensis Leaf Extract, Panthenol, Tropolone, Ascorbyl Glucoside, Allantoin, Lactobacillus/Soybean Extract Ferment Filtrate, Nicotinoyl Hexapeptide-44, Adenosine

PURPOSE

Purpose: Skin Protectant

Cautions

Cautions: For external use only. Avoid contact with eyes and mouth. Discountinue use if signs of irritation or rashes appear. Keep out of reach of children. Replace the cap after use.

KEEP OUT OF REACH OF CHILDREN

INDICATIONS & USAGE

How to use: After using Toner and essence gently apply on entire face and tap for better absorption.

DOSAGE & ADMINISTRATION

How to use: After using Toner and essence gently apply on entire face and tap for better absorption.